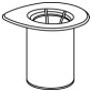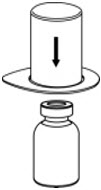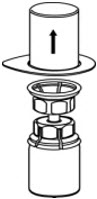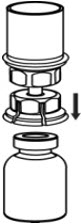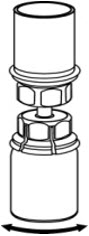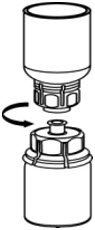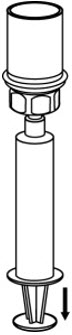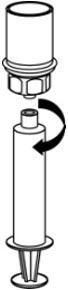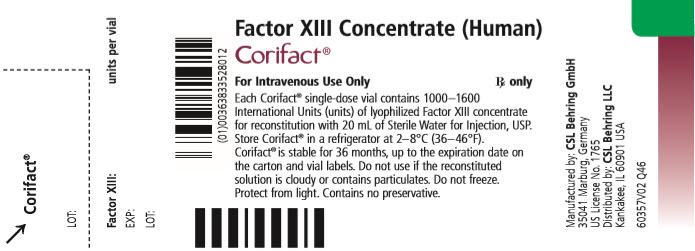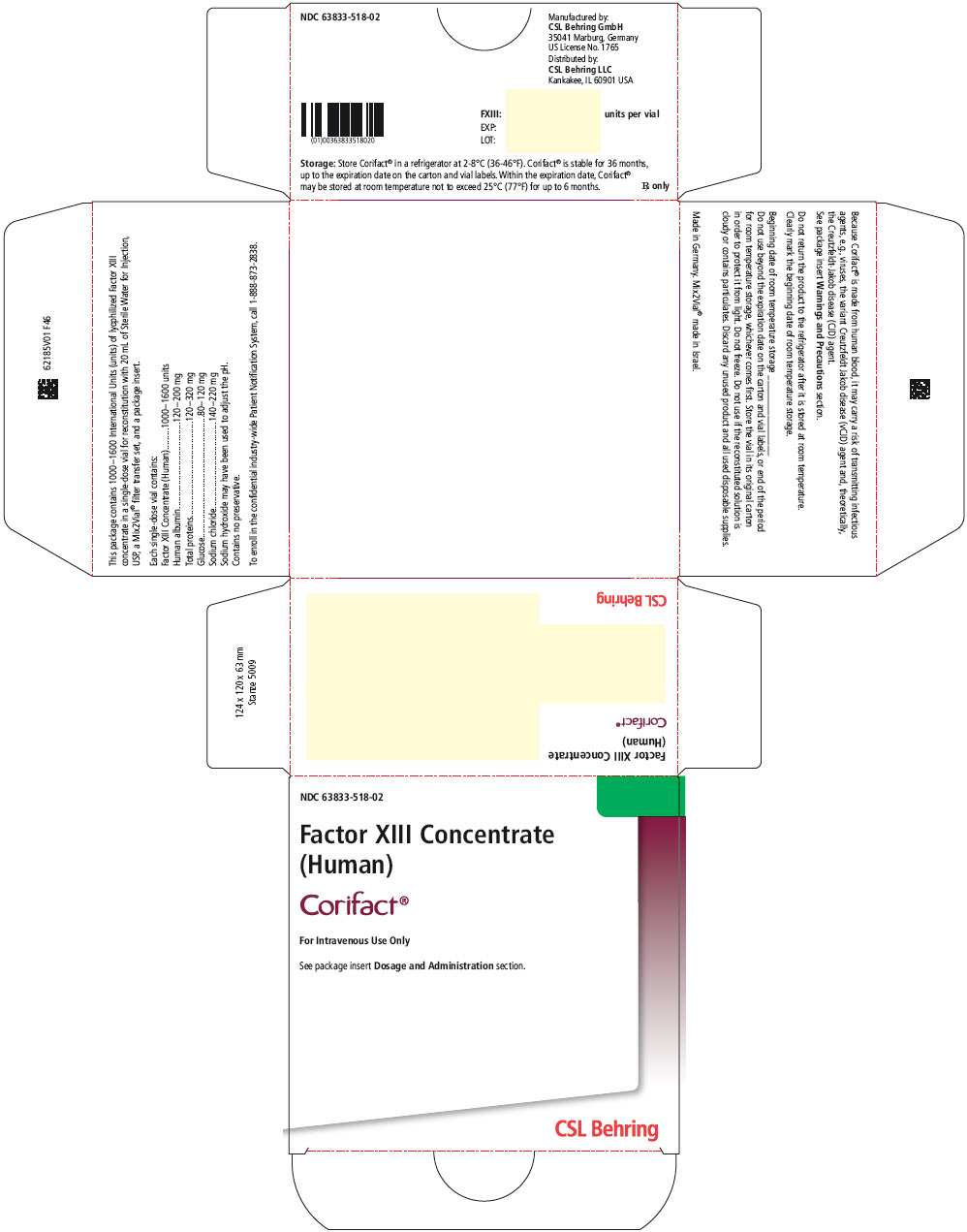 DRUG LABEL: Corifact
NDC: 63833-518 | Form: KIT | Route: INTRAVENOUS
Manufacturer: CSL Behring GmbH
Category: other | Type: PLASMA DERIVATIVE
Date: 20200818

ACTIVE INGREDIENTS: Factor XIII Concentrate (Human) 1600 [iU]/20 mL
INACTIVE INGREDIENTS: Albumin Human 200 [iU]/20 mL; Sodium Chloride; Sodium Hydroxide; Water

HIGHLIGHTS OF PRESCRIBING INFORMATION

These highlights do not include all the information needed to use CORIFACT safely and effectively. See full prescribing information for CORIFACT.
CORIFACT®, Factor XIII Concentrate (Human)
Lyophilized powder for solution for injection
For intravenous use only.
Initial U.S. Approval: 2011

1 INDICATIONS AND USAGE

CORIFACT is a Factor XIII concentrate indicated for adult and pediatric patients with congenital Factor XIII deficiency for:

- Routine prophylactic treatment
- Peri-operative management of surgical bleeding. (1)

2 DOSAGE AND ADMINISTRATION

For intravenous use only.

Dose (2.1)

- 40 International Units (IU) per kg body weight; rate not to exceed 4 mL per min.
- Adjust dose ±5 IU per kg to maintain 5% to 20% trough level of FXIII activity.

Dose Adjustment Using the Berichrom Activity Assay (2.1)

FXIII Activity Trough Level (%) | Dosage Change
One trough level of <5% | Increase by 5 IU per kg
Trough level of 5% to 20% | No change
Two trough levels of >20% | Decrease by 5 IU per kg
One trough level of >25% | Decrease by 5 IU per kg

Administration (2.2)

- Administer at a rate not exceeding 4 mL per minute
- For routine prophylaxis, administer every 28 days
- For peri-operative management of surgical bleeding, individualize dose based on the patient's FXIII activity level, type of surgery, and clinical response
- Following are dose adjustment examples for peri-operative management in reference to the patient's last prophylactic dose:

Dose Adjustment for Peri-operative Management

Time Since Last Dose | Dose
Within 7 days | Additional dose may not be needed
8 – 21 days | Additional partial or full dose may be needed based on FXIII activity level
21 – 28 days | Full prophylactic dose

3 DOSAGE FORMS AND STRENGTHS

Each single-dose vial contains 1000-1600 units of lyophilized powder for reconstitution. (3)

4 CONTRAINDICATIONS

Do not use in patients with known anaphylactic or severe systemic reactions to human plasma-derived products. (4)

5 WARNINGS AND PRECAUTIONS

- Hypersensitivity reaction may occur. (5.1)
- Inhibitory antibodies have been detected in patients receiving CORIFACT. (5.2)
- Thrombotic events have been reported with CORIFACT. (5.3)
- Because CORIFACT is made from human blood, it may carry a risk of transmitting infectious agents, e.g., viruses, the variant Creutzfeldt-Jakob disease (vCJD) agent and, theoretically, the Creutzfeldt-Jakob Disease (CJD) agent. (5.4)

6 ADVERSE REACTIONS

- The most common adverse reactions reported in clinical trials (>1%) were joint inflammation, hypersensitivity, rash, pruritus, erythema, hematoma, arthralgia, headache, elevated thrombin-antithrombin levels, and increased blood lactate dehydrogenase. (6)
- Serious adverse reactions reported in clinical trials were hypersensitivity, acute ischemia, and neutralizing antibodies against FXIII. (5.1, 6)

To report SUSPECTED ADVERSE REACTIONS, contact the CSL Behring Pharmacovigilance Department at 1-866-915-6958 or FDA at 1-800-FDA-1088 or www.fda.gov/medwatch.

8 USE IN SPECIFIC POPULATIONS

Pediatric: Shorter half-life and faster clearance compared to adults. Dose adjustment may be needed. (8.4)

FULL PRESCRIBING INFORMATION

1 INDICATIONS AND USAGE

CORIFACT is a Factor XIII Concentrate indicated for routine prophylactic treatment and peri-operative management of surgical bleeding in adult and pediatric patients with congenital FXIII deficiency.

2 DOSAGE AND ADMINISTRATION

2.1 Dose

- 40 International Units (IU) per kg body weight at a rate not to exceed 4 mL per minute
- Adjust dose ±5 IU per kg to maintain 5% to 20% trough level of FXIII activity as provided in the example below

Table 1. Dose Adjustment Using the Berichrom Activity Assay
FXIII Activity Trough Level (%) | Dosage Change
One trough level of <5% | Increase by 5 IU per kg
Trough level of 5% to 20% | No change
Two trough levels of >20% | Decrease by 5 IU per kg
One trough level of >25% | Decrease by 5 IU per kg

2.2 Administration

- Administer at a rate not exceeding 4 mL per minute
- For routine prophylaxis, administer every 28 days
- For peri-operative management of surgical bleeding:
  - Dosing should be individualized based on the patient's FXIII activity level, type of surgery, and clinical response
  - Monitor patient's FXIII activity levels during and after surgery
  - Following are dose adjustment examples for peri-operative management in reference to the patient's last prophylactic dose:

Table 2. Dose Adjustment for Peri-operative Management
Time Since Last Dose | Dose
Within 7 days | Additional dose may not be needed
8 – 21 days | Additional partial or full dose may be needed based on FXIII activity level
21 – 28 days | Full prophylactic dose

The potency expressed in International Units is determined using the Berichrom activity assay, referenced to the current International Standard for Blood Coagulation Factor XIII, Plasma.

2.3 Reconstitution

Perform a visual inspection of the reconstituted solution. Parenteral drug products should be inspected visually for particulate matter and discoloration prior to administration, whenever solution and container permit.

The procedures below are provided as general guidelines for the preparation and reconstitution of CORIFACT.

Reconstitute CORIFACT at room temperature as follows:

1. Ensure that the CORIFACT vial and diluent vial are at room temperature.
2. Place the CORIFACT vial, diluent vial, and Mix2Vial® transfer set on a flat surface.
3. Remove CORIFACT and diluent vial flip caps. Wipe the stoppers with an alcohol swab and allow the stoppers to dry prior to opening the Mix2Vial transfer set package.
4. Open the Mix2Vial transfer set package by peeling away the lid (Fig. 1). Leave the Mix2Vial transfer set in the clear package.
  Fig. 1
5. Place the diluent vial on a flat surface and hold the vial tightly. Grip the Mix2Vial transfer set together with the clear package and push the plastic spike at the blue end of the Mix2Vial transfer set firmly through the center of the stopper of the diluent vial (Fig. 2).
  Fig. 2
6. Carefully remove the clear package from the Mix2Vial transfer set. Make sure that you pull up only the clear package, not the Mix2Vial transfer set (Fig. 3).
  Fig. 3
7. With the CORIFACT vial placed firmly on a flat surface, invert the diluent vial with the Mix2Vial transfer set attached and push the plastic spike of the transparent adapter firmly through the center of the stopper of the CORIFACT vial (Fig. 4). The diluent will automatically transfer into the CORIFACT vial.
  Fig. 4
8. With the diluent and CORIFACT vial still attached to the Mix2Vial transfer set, gently swirl the CORIFACT vial to ensure that the CORIFACT is fully dissolved (Fig. 5). Do not shake the vial.
  Fig. 5
9. With one hand, grasp the CORIFACT side of the Mix2Vial transfer set and with the other hand grasp the blue diluent-side of the Mix2Vial transfer set, and unscrew the set into two pieces (Fig. 6).
  Fig. 6
10. Draw air into an empty, sterile syringe. While the CORIFACT vial is upright, screw the syringe to the Mix2Vial transfer set. Inject air into the CORIFACT vial. While keeping the syringe plunger pressed, invert the system upside down and draw the concentrate into the syringe by pulling the plunger back slowly (Fig. 7).
  Fig. 7
11. Now that the concentrate has been transferred into the syringe, firmly grasp the barrel of the syringe (keeping the plunger facing down) and unscrew the syringe from the Mix2Vial transfer set (Fig. 8). Attach the syringe to a suitable intravenous administration set.
  Fig. 8
12. If patient requires more than one vial, pool the contents of multiple vials into one syringe. Use a separate unused Mix2Vial transfer set for each product vial.
13. CORIFACT is for dose use only. Contains no preservatives. The product must be used within 4 hours after reconstitution. Do not refrigerate or freeze the reconstituted solution. Discard partially used vials.

3 DOSAGE FORMS AND STRENGTHS

CORIFACT is available as lyophilized powder in a single-dose vial containing 1000-1600 units of Factor XIII concentrate for reconstitution. A 20 mL vial of Sterile Water for Injection, USP, is provided for reconstitution.

The actual units of potency of FXIII are stated on each CORIFACT vial label and carton.

4 CONTRAINDICATIONS

CORIFACT is contraindicated in patients with known anaphylactic or severe systemic reactions to human plasma-derived products [see Description (11)].

5 WARNINGS AND PRECAUTIONS

5.1 Hypersensitivity

Hypersensitivity reactions have been observed with CORIFACT. If signs or symptoms of anaphylaxis or hypersensitivity reactions (including urticaria, rash, tightness of the chest, wheezing, hypotension) occur, immediately discontinue administration [see Patient Counseling Information (17)] and institute appropriate treatment.

5.2 Immunogenicity

Development of inhibitory antibodies against FXIII has been detected in patients receiving CORIFACT. Monitor patients for development of inhibitory antibodies. Presence of inhibitory antibodies may manifest as an inadequate response to treatment. If expected plasma FXIII activity levels are not attained, or if breakthrough bleeding occurs while receiving prophylaxis, perform an assay that measures FXIII inhibitory antibody concentrations.

5.3 Thromboembolic Risk

Thromboembolic complications have been reported. Monitor patients with known risk factors for thrombotic events.

5.4 Transmission of Infectious Agents

Because CORIFACT is made from human blood, it may carry a risk of transmitting infectious agents, e.g., viruses, the variant Creutzfeldt-Jakob disease (vCJD) agent and, theoretically, the Creutzfeldt-Jakob disease (CJD) agent. This also applies to unknown or emerging viruses and other pathogens.

All infections thought by a physician to have been possibly transmitted by this product are to be reported by the physician or other healthcare provider to the CSL Behring Pharmacovigilance Department at 1-866-915-6958 or FDA at 1-800-FDA-1088 or www.fda.gov/medwatch.

5.5 Monitoring Laboratory Tests

- Monitor patient's trough FXIII activity level during treatment with CORIFACT [see Dosage and Administration (2.2)].
- If breakthrough bleeding occurs, or if expected peak plasma FXIII activity levels are not attained, perform an investigation to determine the presence of FXIII inhibitory antibodies [see Clinical Pharmacology (12.3)].

6 ADVERSE REACTIONS

The most common adverse reactions reported in clinical trials (>1%) are joint inflammation, hypersensitivity, rash, pruritus, erythema, hematoma, arthralgia, headache, elevated thrombin-antithrombin levels, and increased blood lactate dehydrogenase.

The serious adverse reactions, reported (frequency 0.5%), were hypersensitivity, acute ischemia, and neutralizing antibodies against FXIII [see Warnings and Precautions 5)].

6.1 Clinical Trials Experience

Because clinical trials are conducted under widely varying conditions, adverse reaction rates observed in the clinical trials of a drug cannot be directly compared to rates in the clinical trials of another drug and may not reflect the rates observed in practice.

Twelve clinical studies included a total of 188 subjects, 108 subjects were <16 years of age [see Use in Specific Populations (8.4)] and a total of approximately 4314 infusions of CORIFACT were administered in the studies. The most common adverse reactions occurring at a rate of 1-2% are outlined [see Adverse Reactions (6)].

6.2 Immunogenicity

A case of neutralizing antibodies against FXIII was reported in an open enrollment clinical study. The patient received prophylactic treatment with CORIFACT for ten years. Concomitant medications included interferon for hepatitis C infection. This patient presented with bruising, and post-infusion FXIII levels were found to be lower than expected. Over several weeks, FXIII recovery values decreased, so the dose and frequency of treatments were increased. Neutralizing antibodies to FXIII were detected, interferon treatment was discontinued, and the subject underwent plasmapheresis. Within a month, neutralizing antibodies were no longer detectable, FXIII recovery levels improved, and the previous prophylactic regimen was resumed.

8 USE IN SPECIFIC POPULATIONS

8.1 Pregnancy

Risk Summary

Animal reproduction studies have not been conducted with CORIFACT.

In the U.S. general population, the estimated background risk of major birth defects and miscarriage in clinically recognized pregnancies is 2-4% and 15-20%, respectively.

Clinical Considerations: Disease-associated maternal and/or embryo/fetal risk

Miscarriage is a known complication of congenital FXIII deficiency with a rate of 91% observed in 136 pregnancies without routine FXIII supplementation prophylaxis and 11% in 45 pregnancies with routine FXIII prophylaxis^1.

8.2 Lactation

Risk Summary

There is no information available on the presence of CORIFACT in human milk, the effects on the breastfed child, or the effects on milk production. The developmental and health benefits of breastfeeding should be considered along with the mother's clinical need for CORIFACT and any potential adverse effects on the breastfed child from CORIFACT or from the underlying maternal condition.

8.4 Pediatric Use

Of the 188 subjects in the CORIFACT clinical studies, 108 were subjects <16 years of age at the time of enrollment (see Table 3).

Table 3. Pediatric Subjects in CORIFACT Clinical Studies
Age Group | Subjects (n)
<1 month | 2
1 month to <2 years | 16
2 to 11 years | 60
12 to <16 years | 30

In the pharmacokinetic study [see Clinical Pharmacology (12.3)], 5 of the 14 subjects ranged in age from 2 to <16 years. Subjects less than 16 years had a shorter half-life (5.7 ± 1.00 days) and faster clearance (0.29 ± 0.12 mL/hr/kg) compared to adults (half-life: 7.1 ± 2.74 days, clearance: 0.22 ± 0.07 mL/hr/kg). Dose adjustments may be needed for patients <16 years of age. There were no differences in the safety profile in children as compared to adults.

8.5 Geriatric Use

Clinical studies of CORIFACT did not include subjects aged 65 and over to determine whether they respond differently from younger subjects. In general, dose selection for an elderly patient should be cautious, usually starting at the low end of the dosing range, reflecting the greater frequency of decreased hepatic, renal, or cardiac function, and of concomitant disease or another drug therapy.

11 DESCRIPTION

CORIFACT, Factor XIII Concentrate (Human), is a heat-treated, lyophilized concentrate of coagulation factor XIII for reconstitution for intravenous use. CORIFACT (FXIII) consists of two A-subunits and two B-subunits, and is made from pooled human plasma. Each vial contains 1000-1600 units FXIII, 120 to 200 mg human albumin, 120 to 320 mg total protein, 80 to 120 mg glucose and 140 to 220 mg sodium chloride. Sodium hydroxide may have been used to adjust the pH.

All plasma used in the manufacture of CORIFACT is obtained from US donors and is tested using serological assays for hepatitis B surface antigen and antibodies to HIV-1/2 and HCV. The plasma is tested with Nucleic Acid Testing (NAT) for HCV, HIV-1, HAV and HBV and found to be non-reactive (negative), and the plasma is also tested by NAT for Human Parvovirus B19. Only plasma that passed virus screening is used for production, and the limit for Parvovirus B19 in the fractionation pool is set not to exceed 10^4 International Units of Parvovirus B19 DNA per mL.

CORIFACT is manufactured from cryo-depleted plasma into an ethanol precipitate, which is then purified by the following four steps:

- Precipitation/adsorption
- Ion exchange chromatography
- Heat-treatment (+60°C for 10 hours in an aqueous solution)
- Virus filtration over two 20 nm filters in series

The sterile filtered final bulk solution is filled into vials and lyophilized. These four manufacturing steps were independently validated in a series of in vitro experiments for their capacity to inactivate or remove both enveloped and non-enveloped viruses. Table 4 shows the virus clearance capacity of the CORIFACT manufacturing process, expressed as mean log10 reduction factor.

Table 4. Overall Virus Inactivation/Removal in CORIFACT
Manufacturing Steps | Virus Reduction Factor (log10)
Manufacturing Steps | Enveloped Viruses |  |  |  | Non-Enveloped Viruses
 | HIV | BVDV | WNV | PRV | HAV | CPV
Al(OH)3 Adsorption / Vitacel® and Defibrination | n.d. | n.d. | n.d. | 6.9 | n.d. | n.d.
Ion Exchange Chromatography | 5.0 | 3.3 | n.d. | ≥8.0 | 3.4 | 3.7
Heat Treatment | ≥7.7 | ≥8.1 | ≥7.4 | N/A [Not included in the calculation of the overall virus reduction factor.] | 4.3 | 1.0 [Studies using human parvovirus B19, which are considered experimental in nature, have demonstrated a virus reduction factor of ≥4.0 log10 by heat treatment.]
20 nm / 20 nm Virus Filtration | ≥6.1 | ≥5.0 | ≥7.4 | ≥6.4 | ≥5.6 | 6.1
Cumulative Virus Reduction (log10) | ≥18.8 | ≥16.4 | ≥14.8 | ≥21.3 | ≥13.3 | 10.8
HIV, Human immunodeficiency virus type 1, model for HIV-1 and HIV-2
BVDV, bovine viral diarrhea virus, model for HCV
WNV, West Nile virus
PRV, pseudorabies virus, a model for large enveloped DNA viruses
HAV, Hepatitis A virus
CPV, canine parvovirus, model for B19V
B19V, Human parvovirus B19
N/A, not applicable
n.d., not done

12 CLINICAL PHARMACOLOGY

12.1 Mechanism of Action

CORIFACT (FXIII) is an endogenous plasma glycoprotein consisting of two A-subunits and two B-subunits. FXIIIa promotes cross-linking of fibrin during coagulation and is essential to the physiological protection of the clot against fibrinolysis. FXIIIa is a transglutaminase enzyme that catalyzes the cross-linking of the fibrin α- and γ-chains for fibrin stabilization and renders the fibrin clot more elastic and resistant to fibrinolysis.^2,3 FXIIIa also cross-links α2-plasmin inhibitor to the α-chain of fibrin, resulting in protection of the fibrin clot from degradation by plasmin. Cross-linked fibrin is the end result of the coagulation cascade, and provides tensile strength to a primary hemostatic platelet plug.^3

The B-subunits in plasma have no enzymatic activity, and function as carrier molecules for the A-subunits. They stabilize the structure of the A-subunits and protect them from proteolysis.

12.2 Pharmacodynamics

Administration of CORIFACT to patients with congenital FXIII deficiency replaces missing or low levels of coagulation Factor XIII, enabling a temporary correction of the factor deficiency and correction of bleeding tendencies. There are no markers that can quantitatively assess the in vivo pharmacodynamics of FXIII. The results of standard coagulation (clot time-based) tests are normal in FXIII deficient patients as it is the quality of the clot that is affected. A qualitative assay of clot suitability is used as an indicator of FXIII deficiency; when performed correctly the test is positive only when the FXIII activity in the sample is close to zero. Thromboelastography can also be affected by FXIII deficiency.

12.3 Pharmacokinetics

A 12-week prospective, open-label, multicenter pharmacokinetic and safety study was conducted in 7 females and 7 males with congenital FXIII deficiency, ranging in age from 5 to 42 years (3 children, 2 adolescents, 9 adults). One adult male did not complete the pharmacokinetic study.

Each subject received 40 units per kg CORIFACT intravenously every 28 days for a total of three doses administered at approximately 250 units per minute. Blood samples for doses 1 and 2 were drawn from patients to determine the FXIII activity level at baseline and 30 and 60 minutes after the infusion. Following the infusion of the third dose of CORIFACT, blood samples were drawn at regular intervals up to 28 days to determine the pharmacokinetic parameters. The mean increase in FXIII activity levels was 83% with a range of 48 to 114% over the baseline after the third dose. The pharmacokinetic parameters based on baseline adjusted FXIII activity (Berichrom assay) are shown in Table 5.

Table 5. Pharmacokinetic Parameters (n=13) by Berichrom Assay Method - Baseline Adjusted Values
Parameters | Mean ±SD
AUC ss, 0-inf (units∙hr/mL) | 184.0 ±65.78
Css, max (units/mL) [100% activity corresponds to 1 unit/mL] | 0.9 ±0.20
Css, min (units/mL) | 0.05 ±0.05
Tmax (hr) | 1.7 ±1.44
Half-life [days] | 6.6 ±2.29
CL [mL/hr/kg] | 0.25 ±0.09
Vss [mL/kg] | 51.1 ±12.61
MRT [days] | 10.0 ±3.45
AUC ss, (0-inf) = Area under the plasma concentration curve from time 0 to infinity at steady state
Css, max: Peak concentration at steady state
Css, min: Trough concentration at steady state
Tmax: Time to peak concentration
CL: Clearance
Vss: Volume of distribution at steady state
MRT = Mean residence time
SD = Standard deviation

13 NONCLINICAL TOXICOLOGY

13.2 Animal Toxicology and/or Pharmacology

CORIFACT was studied in an acute toxicity study in mice and rats at doses up to 3550 units per kg and 1420 units per kg, respectively. Repeat dose toxicity was studied in rats at daily doses up to 350 units per kg for a period of 14 days. No signs of toxicity were observed in the single dose and repeat dose studies.

A local tolerance study in rabbits demonstrated no clinical or histopathological changes at the injection site after intravenous, intra-arterial or para-venous administration of CORIFACT.

A thrombogenicity test was performed in rabbits at doses up to 350 units per kg. CORIFACT showed no thrombogenic potential at the doses tested.

14 CLINICAL STUDIES

Pharmacokinetic Study

The accelerated approval of CORIFACT was based on a pharmacokinetic study in 13 subjects with congenital FXIII deficiency evaluating three doses at 40 units per kg every 28 days for each subject. Maintaining FXIII activity trough level between 5%-20% is predicted to provide clinical benefit. Twelve out of thirteen subjects (92%) attained trough FXIII levels of ≥ 5%. based on standard Berichrom assay [see Clinical Pharmacology (12.3)].

The post marketing efficacy and safety trial was a prospective, multicenter, open-label study conducted in 41 subjects who received routine prophylactic treatment (40 U/kg every 28 days for 52 weeks) for congenital FXIII deficiency, was to verify the clinical benefit of CORIFACT by showing correlation between trough levels of FXIII activity and bleeding outcomes. The clinical benefit of CORIFACT was also demonstrated by comparing the incidence of bleeding in CORIFACT-treated subjects to historical control with congenital FXIII deficiency. This study included 18 subjects (44%) who were less than 16 years of age and 23 subjects (56%) who were ≥16 to <65 years. Two subjects were 1 month to <2 years of age, 8 subjects were 2 years to <12 years, and 8 subjects were 12-16 years of age.

The incidence of spontaneous bleeding episodes requiring treatment was evaluated. Treatment was defined as an administration of a FXIII-containing product to treat the bleeding episode. None of the 5 subjects who experienced a spontaneous bleeding episode (2 nose bleeds, 2 rectal bleeds, and 1 episode of hematuria associated with a urinary tract infection, and an indwelling urinary catheter) required treatment with a FXIII-containing product.

An annualized bleeding rate of 0 episodes per subject per year for spontaneous bleeding was established when compared to a historical annualized bleeding rate of 2.5 episodes per subject per year in patients receiving on-demand treatment of acute bleeding in patients with congenital FXIII deficiency.^4

Eight bleeding episodes secondary to trauma, and one associated with surgery were also reported during the 52 weeks of the trial. In the eight bleeding episodes secondary to trauma, six did not require treatment with a FXIII-containing product, and two were successfully treated with a FXIII-containing product (one was treated with CORIFACT and one with plasma).

The prophylactic administration of Factor XIII Concentrate (Human) every 28 days in subjects with congenital FXIII deficiency achieved mean FXIII activity levels between 5% and 20%. FXIII activity was maintained at ≥5% in ≥97% of subjects and ≥10% in ≥85% of subjects. Of the 533 doses administered to 41 subjects, dose adjustment was required on only eight occasions, supporting that 40 U/kg every 28 days is the appropriate dose for the majority of patients.

Five subjects underwent surgical procedures, four were elective and one was an emergency. Of the four elective surgeries, three subjects received CORIFACT prior to surgery (0 to 7 days prior to surgery) with no post-operative bleeding. One subject who received CORIFACT 7 days prior to surgery experienced bleeding post-extraction of all four wisdom teeth. The bleeding was stopped four hours after the oral surgery with an additional dose of CORIFACT (50% of the subject's routine dose). One subject who required emergency surgery was pre-treated with plasma.

15 REFERENCES

1. Sharief, LAT., Kadir RA.:Congenital factor XIII deficiency in women: a systemic review of literature, Hemophilia. 2013; 19: e349-e357.
2. Lauer P, Metzner HJ, Zettlmeissl G, Li M, et al. Targeted Inactivation of the Mouse Locus Encoding Coagulation Factor XIII-A: Hemostatic Abnormalities in Mutant Mice and Characterization of the Coagulation Deficit. Thromb Haemost. 2002;88:967-74.
3. Dardik R, Loscalzo J, Inbal A. Factor XIII (FXIII) and Angiogenesis. J Thromb Haemost. 2006;4:19-25.
4. Lusher J, Pipe SW, Alexander S, Nugent D. Prophylactic therapy with Fibrogammin P is associated with a decreased incidence of bleeding episodes: a retrospective study. Haemophilia. 2009;1-6.

16 HOW SUPPLIED/STORAGE AND HANDLING

Table 6. How Supplied
Presentation | Carton NDC Number | Components
1000-1600 units [The actual units of potency of FXIII Concentrate (Human) are stated on each CORIFACT vial label and carton.] | 63833-518-02 | - CORIFACT in a single-dose vial [NDC 63833-528-01] - 20 mL vial of Sterile Water for Injection, USP [NDC 63833-734-65] - Mix2Vial filter transfer set

Storage and Handling

- Refrigerate CORIFACT at 2-8°C (36-46°F). Keep in original carton to protect from light. Do not freeze.
- CORIFACT is stable for 36 months, up to the expiration date on the carton and vial labels. Within the expiration date, CORIFACT may be stored at room temperature not to exceed 25°C (77°F) for up to 6 months.
  - Do not return the product to the refrigerator after it is stored at room temperature. Clearly mark the beginning date of room temperature storage on the carton label.
  - Do not use beyond the expiration date on the carton and vial labels, or end of the period for room temperature storage, whichever comes first.
- This product does not contain a preservative and must be used within 4 hours after reconstitution. Do not refrigerate or freeze the reconstituted solution.
- Discard any unused product and all used disposable supplies.

17 PATIENT COUNSELING INFORMATION

See FDA-approved patient labeling (Patient Product Information)

- Inform patients of the signs and symptoms of allergic hypersensitivity reactions, such as urticaria, rash, tightness of the chest, wheezing, hypotension and/or anaphylaxis experienced during or after injection of CORIFACT [see Warnings and Precautions (5.1)].
- Inform patients of the signs and symptoms of immunogenicity such as breakthrough bleeding [see Warnings and Precautions (5.2)].
- Inform patients of signs and symptoms of thrombosis, such as limb or abdomen swelling and/or pain, chest pain, shortness of breath, loss of sensation or motor power, altered consciousness, vision, or speech [see Warnings and Precautions (5.3)].
- Inform patients that because CORIFACT is made from human blood, it may carry a risk of transmitting infectious agents, e.g., viruses, the variant Creutzfeldt-Jakob disease (vCJD) agent and, theoretically, the Creutzfeldt-Jakob disease (CJD) agent [see Warnings and Precautions (5.4) and Description (11)].

Manufactured by:
CSL Behring GmbH
35041 Marburg Germany
US License No. 1765

Distributed by:
CSL Behring LLC
Kankakee, IL 60901 USA

FDA-Approved Patient Labeling – Patient Product Information (PPI)

CORIFACT®
Factor XIII Concentrate (Human)

This leaflet summarizes important information about CORIFACT. Please read it carefully before using CORIFACT and each time you get a refill. There may be new information provided. This information does not take the place of talking with your healthcare provider, and it does not include all of the important information about CORIFACT. If you have any questions after reading this, ask your healthcare provider.

What is CORIFACT?

CORIFACT is an injectable medicine used for routine prophylactic treatment and peri-operative management of surgical bleeding in adults and pediatric patients with congenital Factor XIII (FXIII) deficiency. CORIFACT is a coagulation FXIII concentrate made from human plasma, and has important functions in hemostasis (stopping of bleeding).

Who should not use CORIFACT?

You should not use CORIFACT if you have experienced hypersensitivity (allergy) reactions, including anaphylactic or severe systemic reactions to human plasma-derived products.

What should I tell my healthcare provider before CORIFACT is given?

Tell your healthcare provider about all of your medical conditions, including:

- If you are pregnant or planning to become pregnant. It has not been established if CORIFACT can harm your unborn baby. Safety and effectiveness in labor and delivery have not been established.
- Breast feeding: It has not been established if CORIFACT passes into your milk.

Tell your healthcare provider and pharmacist about all of the medicines you take, including all prescription and non-prescription medicines such as over-the-counter medicines, supplements, or herbal remedies.

How is CORIFACT given?

CORIFACT is administered into your vein (intravenous injection). Before infusing, CORIFACT is dissolved using sterile water provided in the package. Your healthcare provider will prescribe the dose that you receive.

What could be the possible side effects of CORIFACT?

Call your healthcare provider or the emergency department right away if you have any of the following symptoms after using CORIFACT:

- shortness of breath
- rash
- pruritus (itching)
- erythema (redness of the skin)
- fainting/dizziness
- chest pain
- signs of a blood clot including pain, swelling, warmth, redness, or a lump in your legs or arms.

Other possible side effects may include:

- chills/rise in temperature
- arthralgia (joint pain)
- headache
- breakthrough bleeding and pain resulting from formation of antibodies against CORIFACT.

Because CORIFACT is made from human blood, it may carry a risk of transmitting infectious agents, e.g., viruses, the variant Creutzfeldt-Jakob disease (vCJD) agent and, theoretically, the Creutzfeldt-Jakob (CJD) agent.

These are not all the possible side effects of CORIFACT.

Tell your healthcare provider about any side effect that bothers you or that does not go away. You can also report side effects to the FDA at 1-800-FDA-1088.

What else should I know about CORIFACT?

Medicines are sometimes prescribed for purposes other than those listed here. Do not use CORIFACT for a condition for which it is not prescribed. Do not share CORIFACT with other people, even if they have the same symptoms that you have.

This leaflet summarizes the most important information about CORIFACT. If you would like more information, talk to your healthcare provider. You can ask your healthcare provider or pharmacist for information about CORIFACT that was written for healthcare professionals.

Talk to your healthcare provider before traveling.

Manufactured by:
CSL Behring GmbH
35041 Marburg Germany
US License No. 1765

Distributed by:
CSL Behring LLC
Kankakee, IL 60901 USA

Mix2Vial® is a registered trademark of West Pharma. Services IL, Ltd., a subsidiary of West Pharmaceuticals Services, Inc.

Revised: Month 2020

PRINCIPAL DISPLAY PANEL - 1000-1600 IU Vial Label

Factor XIII Concentrate (Human)

Corifact®

For Intravenous Use Only
Rx only

Each Corifact® single-use vial contains 1000–1600
International Units (units) of lyophilized Factor XIII concentrate
for reconstitution with 20 mL of Sterile Water for Injection, USP.
Store Corifact® in a refrigerator at 2–8°C (36–46°F).
Corifact® is stable for 36 months, up to the expiration date on
the carton and vial labels. Do not use if the reconstituted
solution is cloudy or contains particulates. Do not freeze.
Protect from light. Contains no preservative.

PRINCIPAL DISPLAY PANEL - Kit Carton

NDC 63833-518-02

Factor XIII Concentrate
(Human)

Corifact®

For Intravenous Use Only

See package insert Dosage and Administration section.

CSL Behring